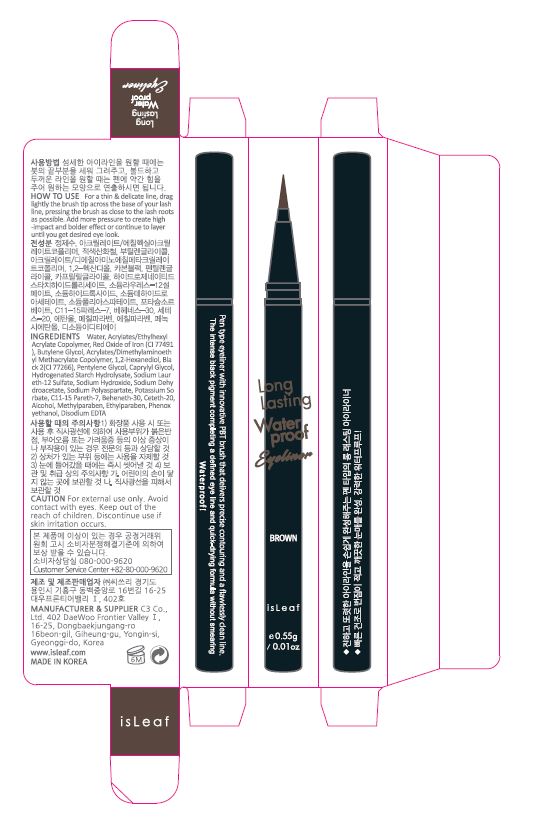 DRUG LABEL: isLeaf Long Lasting Waterproof Eyeliner Brown
NDC: 70818-008 | Form: GEL
Manufacturer: C3 Co., Ltd.
Category: otc | Type: HUMAN OTC DRUG LABEL
Date: 20170826

ACTIVE INGREDIENTS: METHYLPARABEN 0.3 g/100 g
INACTIVE INGREDIENTS: WATER

Drug Facts

ACTIVE INGREDIENT

methylparaben

INACTIVE INGREDIENT

water, butylene glycol, glycerin, alcohol, xanthan gum, etc

PURPOSE

for a tattoo effect

keep out of reach of the children

INDICATIONS AND USAGE

For a thin & delicate line, drag lightly the brush tip across the base of your lash line, pressing the brush as close to the lash roots as possible. To create a thinner line, use less pressure and add more pressure to create high-impact and a bolder line or continue to layer until you get desired eye look

WARNINGS

1. If the following symptoms occur after product use, stop using the product immediately and consult a dermatologist (continuous use can exacerbate the symptoms).
1) Occurrence of red spots, swelling, itchiness, and other skin irritation
2) If the symptoms above occur after the application area is exposed to direct sunlight
2. Do not use on open wounds, eczema, and other skin irritations
3. Precaution for Storage and Handling
1) Close the lid after use
2) Keep out of reach of infants and children
3) Do not to store in a place with high/low temperature and exposed to direct sunlight

4. Use as avoiding eye areas.

DOSAGE AND ADMINISTRATION

for external use only